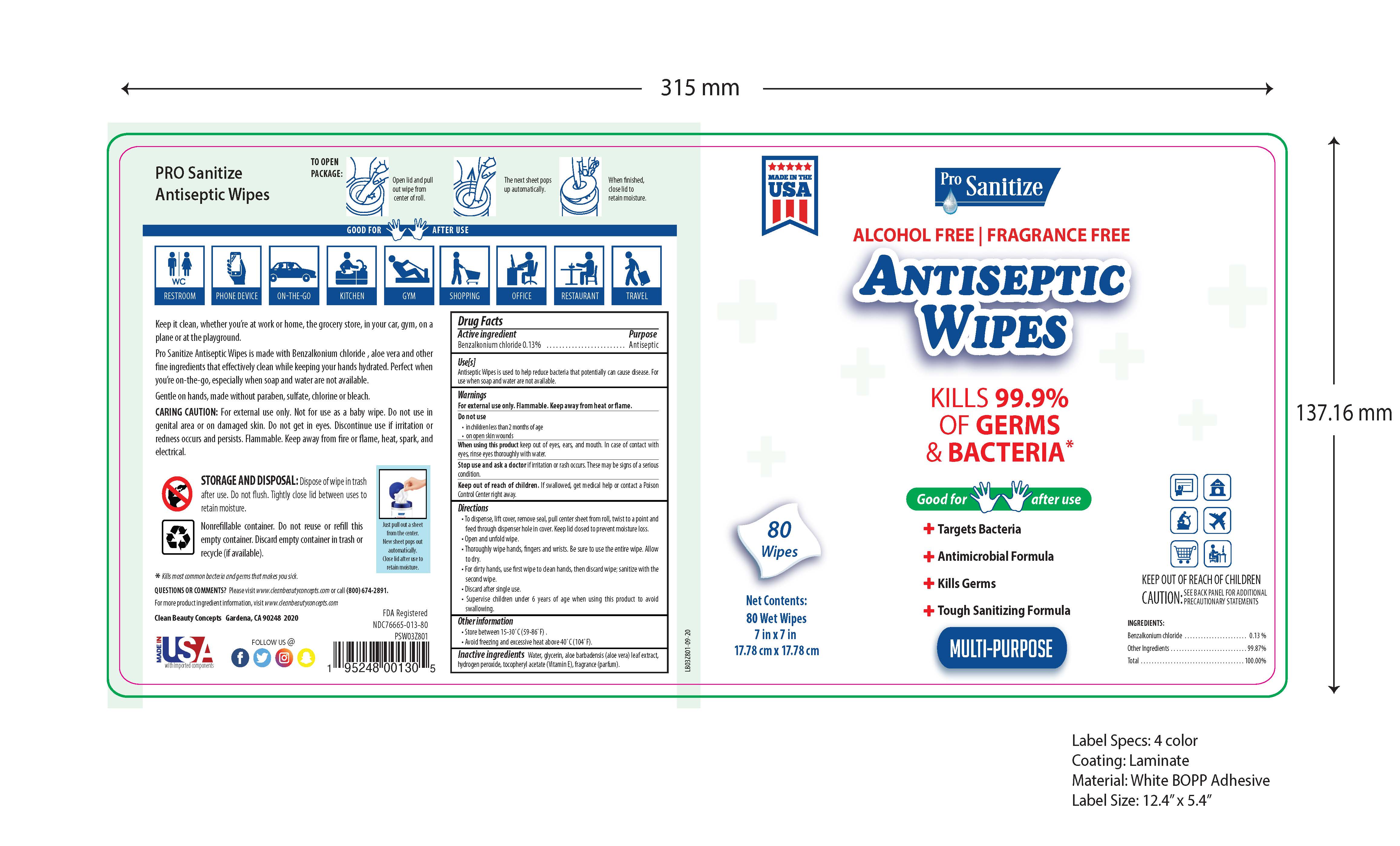 DRUG LABEL: Pro-Sanitize
NDC: 76665-013 | Form: LIQUID
Manufacturer: Clean Beauty Concepts
Category: otc | Type: HUMAN OTC DRUG LABEL
Date: 20201004

ACTIVE INGREDIENTS: BENZALKONIUM CHLORIDE 0.13 mg/100 mL
INACTIVE INGREDIENTS: .ALPHA.-TOCOPHEROL ACETATE 0.1 mL/100 mL; GLYCERIN 1.45 mL/100 mL; HYDROGEN PEROXIDE 0.125 mL/100 mL; WATER 97.895 mL/100 mL; ALOE VERA LEAF 0.3 mL/100 mL

The sanitizer wipes is manufactured using only the following United States Pharmacopoeia (USP) grade ingredients:

1. Benzalkonium Chloride (
2. Glycerol
3. Hydrogen peroxide
4. Sterile distilled water or boiled cold water.
5. Aloe vera leaf extract
6. Vitamin E

Active Ingredient(s)

Benzalkonium Chloride 0.13%

Purpose

Antiseptic

Use

Antiseptic wipes to help reduce bacteria that potentially can cause disease. For use when soap and water are not available

Warnings

For external use only. Flammable. Keep away from heat or flame

Do not use

- in children less than 2 months of age
- on open skin wounds

When using this product keep out of eyes, ears, and mouth. In case of contact with eyes, rinse eyes thoroughly with water.
Stop use and ask a doctor if irritation or rash occurs. These may be signs of a serious condition.
Keep out of reach of children. If swallowed, get medical help or contact a Poison Control Center right away.

Stop use and ask a doctor if irritation or rash occurs. These may be signs of a serious condition.

Keep out of reach of children. If swallowed, get medical help or contact a Poison Control Center right away.

Directions

- To dispense, lift cover, remove seal, pull center sheet from roll, twist to a point and feed through dispenser holde in cover. Keep lid closed to prevent moisture loss.
- Open and unfold wipe
- Thoroughly wipe hands, fingers and wrists. Be sure to use the entire wipe. Allow to dry.
- For dirty hands, use first wipe to clean hands, then discard wipe, sanitize with the second wipe.
- Discard after single use
- Supervise children under 6 years of age when using this product to avoid swallowing

Other information

- Store between 15-30C (59-86F)
- Avoid freezing and excessive heat above 40C (104F)

Inactive ingredients

water(aqua), glycerin, hydrogen peroxide, Aloe Barbadensis, Tocopheryl Acetate Vitamin E

Package Label - Principal Display Panel

80ct NDC: 76665-013-80